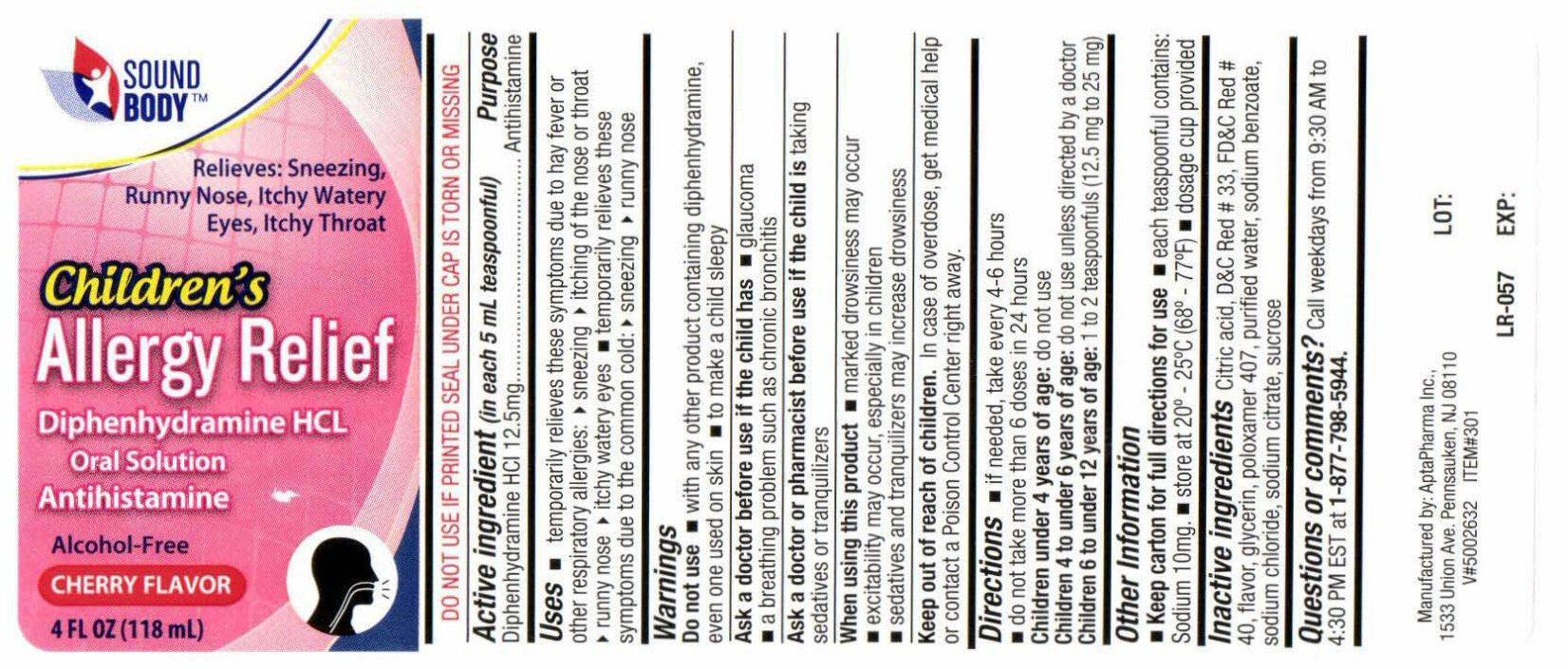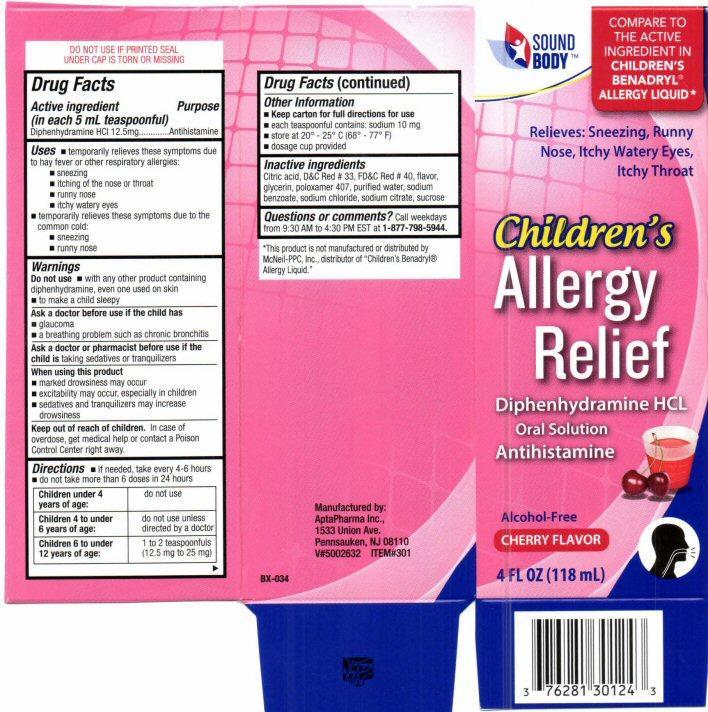 DRUG LABEL: Childrens Allergy Relief
NDC: 76281-301 | Form: LIQUID
Manufacturer: AptaPharma Inc.
Category: otc | Type: HUMAN OTC DRUG LABEL
Date: 20191028

ACTIVE INGREDIENTS: DIPHENHYDRAMINE HYDROCHLORIDE 12.5 mg/5 mL
INACTIVE INGREDIENTS: CITRIC ACID MONOHYDRATE; D&C RED NO. 33; FD&C RED NO. 40; GLYCERIN; POLOXAMER 407; WATER; SODIUM BENZOATE; SODIUM CHLORIDE; SODIUM CITRATE; SUCROSE

Active ingredient

Drug Facts
Active ingredient
(in each 5 mL teaspoon)
Diphenhydramine HCL 12.5 mg

Purpose

Antihistamine

Keep out of reach of children

In case of overdose, get medical help or contact a Poison Control Center right away.

Uses

• temporarily relieves these symptoms due to hay fever or other respiratory allergies:
• sneezing
• itching of the nose or throat
• runny nose
• itchy watery eyes
• temporarily relieves these symptoms due to the common cold:
• sneezing
• runny nose

Warnings

Do not use
• with any other product containing diphenhydramine, even one used on skin
• to make a child sleepy

Ask a doctor before use if the child has

• glaucoma
• a breathing problem such as chronic bronchitis

Ask a doctor or pharmacist before use if the child is

taking sedatives or tranquilizers

When using this product

• marked drowsiness may occur
• excitability may occur, especially in children
• sedatives and tranquilizers may increase drowsiness

Directions

• if needed, take every 4-6 hours
• do not take more than 6 doses in 24 hours
Children under 4 years of age: do not use
Children 4 to under 6 years of age: do not use unless directed by a doctor
Children 6 to under 12 years of age: 1 to 2 teaspoonfuls
(12.5 mg to 25 mg)

Other information

• Keep carton for full directions for use
• each teaspoonful contains: sodium 10 mg
• store at 20-25 ° C (68-77 ° F)
• dosage cup provided

Inactive ingredients

Citric acid, D and C Red # 33, FD and C Red # 40, flavor, glycerin, poloxamer 407, purified water, sodium benzoate, sodium chloride, sodium citrate, sucrose

Questions or comments?

Call weekdays from 9:30 AM to 4:30 PM EST at
1-877-798-5944

Product Label

SOUND BODY™
COMPARE TO THE ACTIVE INGREDIENT IN CHILDREN'S BENADRYL® ALLERGY LIQUID*

Relieves: Sneezing, Runny Nose, Itchy Watery Eyes, Itchy Throat

Children’s
Allergy
Relief

Diphenhydramine HCL Oral Solution Antihistamine
Alcohol-free
Cherry Flavor
4 FL OZ (118 mL)
DO NOT USE IF PRINTED SEAL UNDER CAP IS TORN OR MISSING
Manufactured by:
AptaPharma Inc.
1533 Union Ave.
Pennsauken, NJ 08110

V#5002632 ITEM#301

BX-034

LOT:
EXP:

res